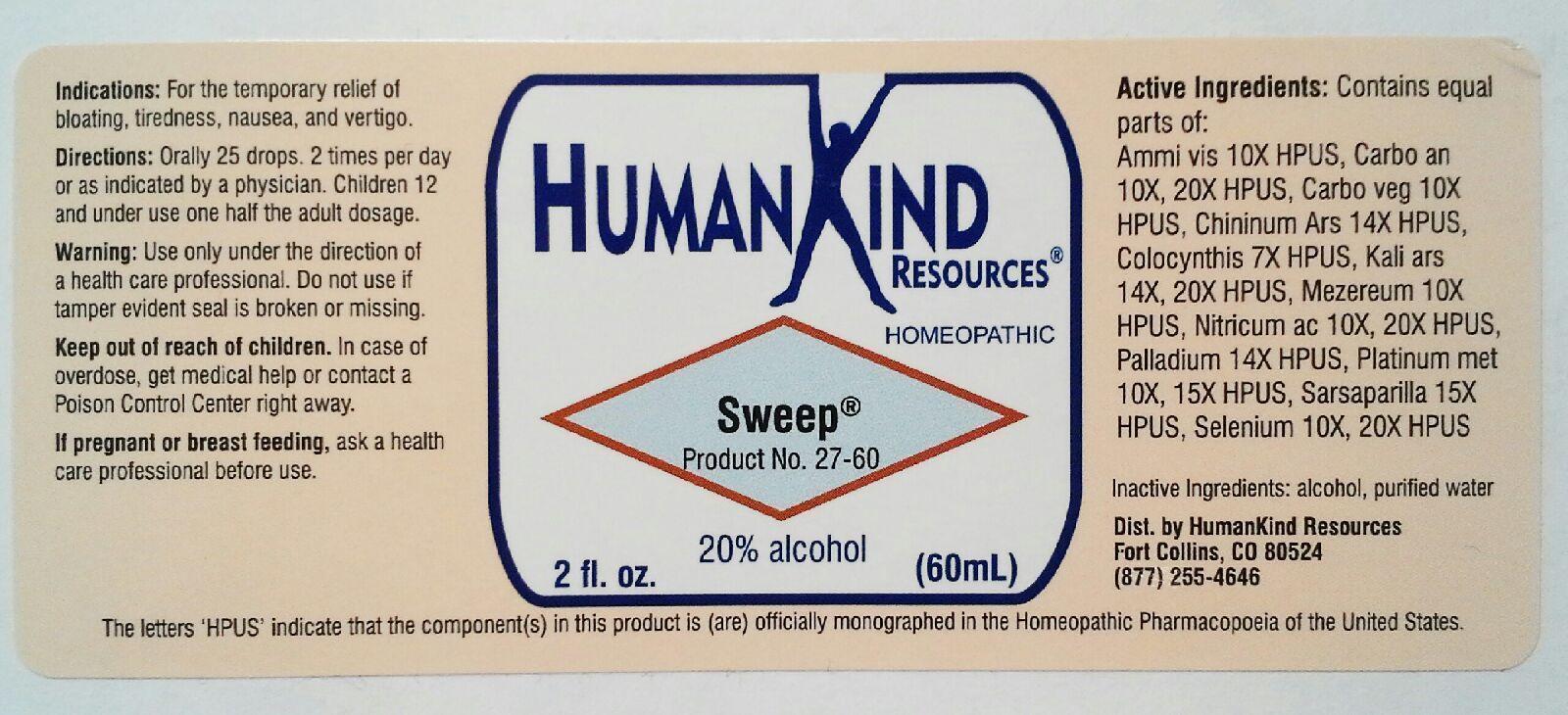 DRUG LABEL: Sweep
NDC: 64616-105 | Form: LIQUID
Manufacturer: Vitality Works, Inc.
Category: homeopathic | Type: HUMAN OTC DRUG LABEL
Date: 20251217

ACTIVE INGREDIENTS: AMMI VISNAGA FRUIT 10 [hp_X]/1 mL; CARBO ANIMALIS 20 [hp_X]/1 mL; ACTIVATED CHARCOAL 10 [hp_X]/1 mL; QUININE ARSENATE 14 [hp_X]/1 mL; CITRULLUS COLOCYNTHIS FRUIT PULP 7 [hp_X]/1 mL; POTASSIUM ARSENITE ANHYDROUS 20 [hp_X]/1 mL; DAPHNE MEZEREUM BARK 10 [hp_X]/1 mL; NITRIC ACID 20 [hp_X]/1 mL; PALLADIUM 14 [hp_X]/1 mL; PLATINUM 15 [hp_X]/1 mL; SARSAPARILLA 15 [hp_X]/1 mL; SELENIUM 20 [hp_X]/1 mL
INACTIVE INGREDIENTS: ALCOHOL; WATER

Sweep

Sweep

Ammi Visnaya 10X Mezereum 10X

Carbo Animalis 10X, 20X Nitricum Acidum 10X, 20X

Carbo Vegetabilis 10X Palladium Metallicum 14X

Chininum Arsenicum 14X Platinum Metallicum 10X, 15X

Colocynthis 7X Sarasparilla 15X

Kali Arsenicosum 14X, 20X Selenium Metallicum 10X, 20X

Sweep

Alcohol, Purified Water

Sweep

Use only under the drection of a health care professional. Do not use if tamper evident seal is broken or missing.

Sweep

Keep out of reach of children. In case of overdose, get medical help or contact a Poison Control Center right away.

Sweep

For the temprory relief of bloating, tiredness, nausea and vertigo.

Sweep

Orally 25 drops, 2 times per day or as indicated by a physician. Children 12 and under use one half the adult dosage.

Sweep

Helps in the detoxification of the body